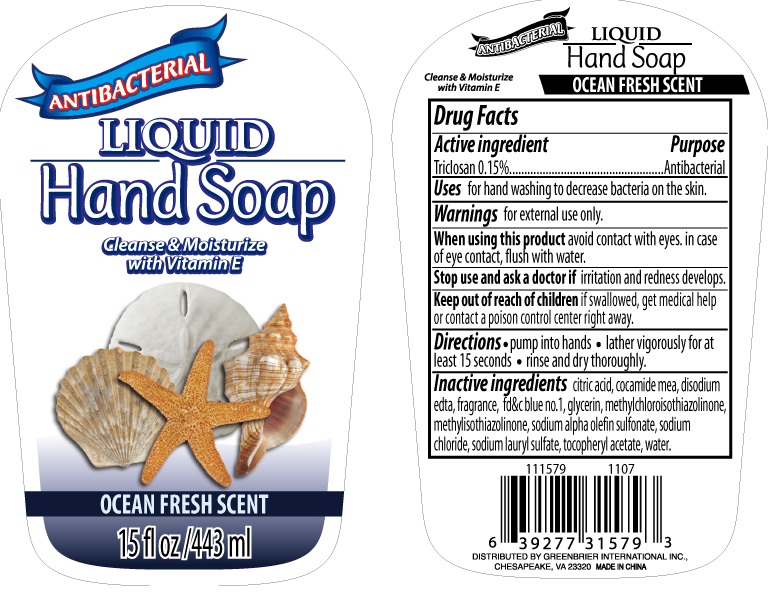 DRUG LABEL: Antibacterial Hand - Ocean Fresh Scent
NDC: 33992-1579 | Form: SOAP
Manufacturer: Greenbrier International, Inc.
Category: otc | Type: HUMAN OTC DRUG LABEL
Date: 20110519

ACTIVE INGREDIENTS: TRICLOSAN 0.15 mL/100 mL
INACTIVE INGREDIENTS: CITRIC ACID MONOHYDRATE; COCO MONOETHANOLAMIDE; EDETATE DISODIUM; FD&C BLUE NO. 1; GLYCERIN; METHYLCHLOROISOTHIAZOLINONE; METHYLISOTHIAZOLINONE; SODIUM CHLORIDE; SODIUM LAURYL SULFATE; ACETATE ION; WATER

Antibacterial Liquid Hand Soap - Ocean Fresh Scent

Active Ingredient

Triclosan 0.15%

Purpose

Antibacterial

Uses

for hand washing to decrease bacteria on the skin.

Warnings

for external use only.

When using this product

avoid contact with eyes. in case of eye contact, flush with water.

Stop use and ask a doctor if

irritation and redness develops

Keep out of reach of children.

if swallowed, get medical help or contact a poison control center right away.

Directions

pump into hands.

lather vigorously for at least 15 seconds

rinse and dry thoroughly

Inactive Ingredients

citric acid, cocamide mea, disodium edta, fragrance fd and c blue no. 1, glycerin, methylchloroisothiazolinone, methylisothiazolinone, sodium alpha olefin sulfonate, sodium chloride, sodium lauryl sulfate, tocopheryl acetate, water.

PACKAGE LABEL

Antibacterial Liquid Hand Soap

Cleans and Moisturize with Vitamin E

Ocean Fresh Scent

15fl oz/443ml

DISTRIBUTED BY GREENBRIER INTERNATIONAL, INC

CHESAPEAKE, VA 23320

MADE IN CHINA